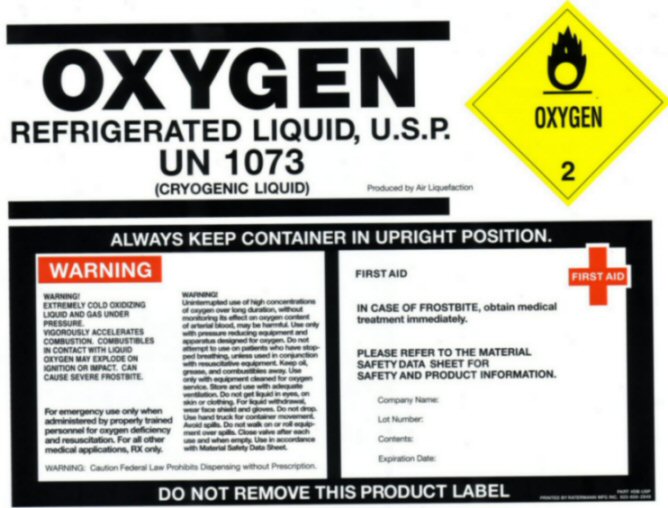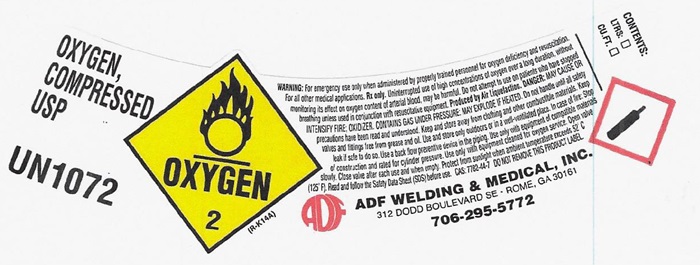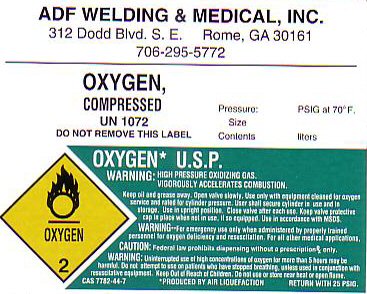 DRUG LABEL: Oxygen
NDC: 64922-233 | Form: GAS
Manufacturer: ADF Welding & Medical, Inc.
Category: prescription | Type: HUMAN PRESCRIPTION DRUG LABEL
Date: 20241002

ACTIVE INGREDIENTS: Oxygen 99 L/100 L

Oxygen

Oxygen Shoulder Label

OXYGEN, COMPRESSED USP UN 1072 OXYGEN 2 (R-K14A)

WARNING: For emergency use only when administered by properly trained personnel for oxygen deficiency and resuscitation. For all other medical applications, Rx only. Uninterrupted use of high concentrations of oxygen over a long duration, without monitoring its effect on oxygen content of arterial blood, may be harmful. Do not attempt to use on patients who have stopped breathing unless used in conjunction with resuscitative equipment. Produced by Air Liquefaction. DANGER: MAY CAUSE OR INTENSIFY FIRE; OXIDIZER. CONTAINS GAS UNDER PRESSURE; MAY EXPLODE IF HEATED. Do not handle until all safety precautions have been read and understood. Keep and store away from clothing and other combustible materials. Keep valves and fittings free from grease and oil. Use and store only outdoors or in a well-ventilated place. In case of fire: Stop leak if safe to do so. Use a back flow preventive device in the piping. Use only with equipment of compatible materials of construction and rated for cylinder pressure. Use only with equipment cleaned for oxygen service. Open valve slowly. Close valve after each use and when empty. Protect from sunlight when ambient temperature exceeds 52°C (125° F). Read and follow the Safety Data Sheet (SDS) before use. CAS 7782-44-7 DO NOT REMOVE THIS PRODUCT LABEL.

CONTENTS: LTRS __ CU.FT. ___

ADF WELDING & MEDICAL, INC.

312 DODD BOULEVARD SE • ROME, GA 30161 • 706-295-5772

Oxygen Body Label

ADF WELDING & MEDICAL, INC

312 Dodd Blvd. S.E. Rome, GA 30161

706-295-5772

OXYGEN, COMPRESSED UN 1072

DO NOT REMOVE THIS LABEL

Pressure: PSIG at 70°F

Size

Contents: Liters

OXYGEN2

OXYGEN* U.S.P.

WARNING: HIGH PRESSUREOXIDIZING GAS. VIGOROUSLY ACCELERATES COMBUSTION.

Keep oil and grease away. Open valve slowly. Use only with equipment cleaned for oxygen service and rated for cylinder pressure. User shall secure cylinder in use and in storage. Use in upright position. Close valve after each use. Keep valve protective cap in place when not in use, if so equipped. Use in accordance of MSDS.

WARNING: For emergency use only when administered by properly trained personnel for oxygen deficiency and resuscitation. For all other medical applications.

CAUTION: Federal law prohibits dispensing without a prescription, Rx only.

WARNING: Uninterrupted use of high concentration of oxygen for more than 5 hours may be harmful. Do not attempt to use on patients who have stopped breathing, unless in conjunction with resuscitative equipment. Keep Out of Reach of Children. Do not use or store near heat or open flame. CAS 7782-44-7 *PRODUCED BY AIR LIQUEFACTION RETURN WITH 25 PSIG

Oxygen Refrigerated

OXYGEN

REFRIGERATED LIQUID, U.S.P.
UN 1073

(CRYOGENIC LIQUID) Produced by Air Liquefaction
OXYGEN 2
ALWAYS KEEP CONTAINER IN UPRIGHT POSITION
WARNING

EXTREMELY COLD OXIDIZING LIQUID AND GAS UNDER PRESSURE. VIGOROUSLY ACCELERATES COMBUSTION. COMBUSIBLES IN CONTACT WITH LIQUID OXYGEN MAY EXPLODE ON IGNIGION OR IMPACT. CAN CAUSE SEVERE FROSTBITE.

For emergency use only when administered by properly trained personnel for
oxygen deficiency and resuscitation. For all other medical applications
RX only.

WARNING! Uninterrupted use of high concentrations of oxygen over long duration,
without monitoring its effect on oxygen content of arterial blood, may
be harmful. Use only with pressure reducing equipment and apparatus
designed for oxygen. Do not attempt to use on patients who have stopped
breathing, unless used in conjunction with resuscitative equipment.
Keep oil, grease, and combustibles away. Use only with equipment
cleaned for oxygen service. Store and use with adequate ventilation. Do
not get liquid in eyes, on skin or clothing. For liquid withdrawal,
wear face shield and gloves. Do not drop. Use hand truck for container
movement. Avoid spills. Do not walk on or roll equipment over spills.
Close valve after each use and when empty. Use in accordance with
Material Safety Data Sheet.

WARNING: Caution Federal Law Prohibits Dispensing without Prescription
FIRST AID

IN CASE OF FROSTBITE, obtain medical treatment immediately.

PLESE REFER T THE MATEERIAL SAFETY DAT SHEET FOR SAFETY AND PRODUCT INFORMATION.

DO NOT REMOVE THIS PRODUCT LABEL